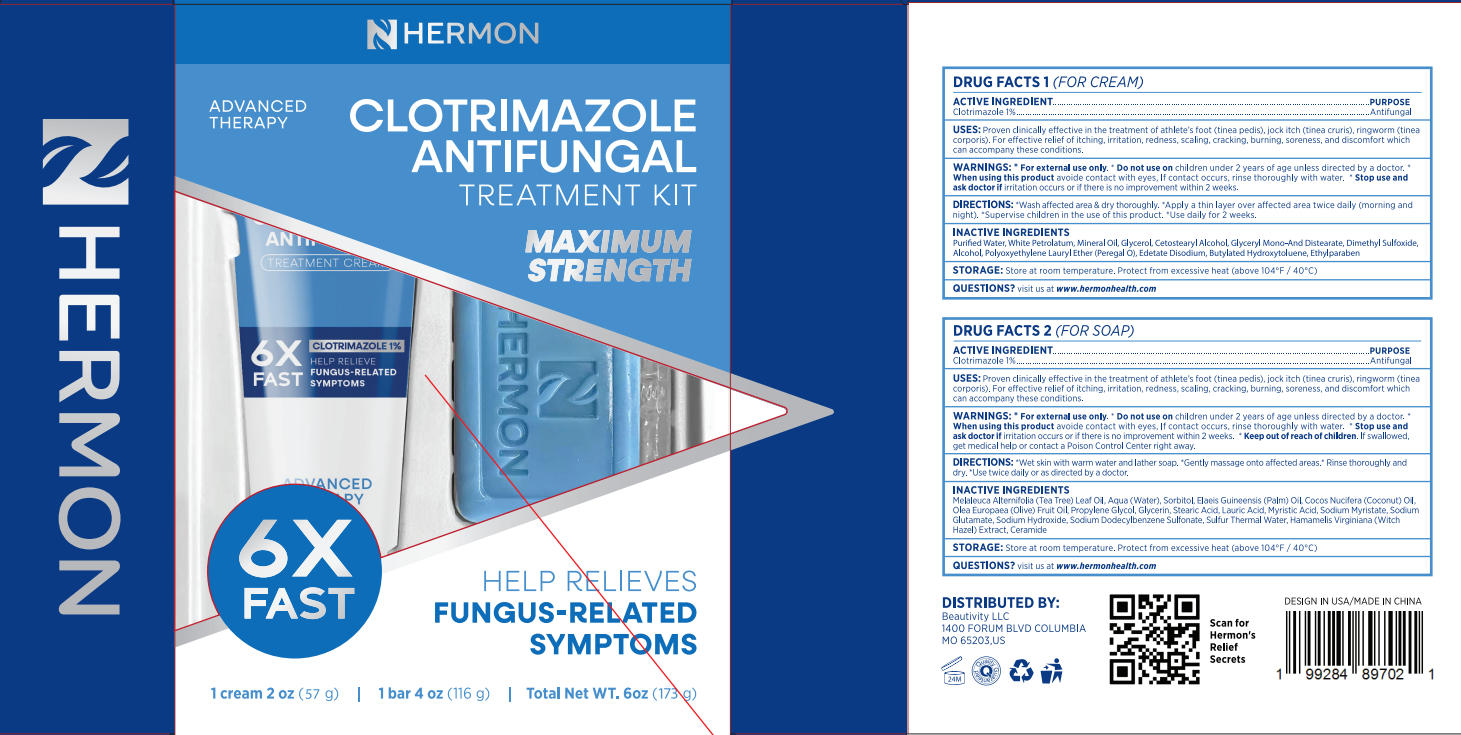 DRUG LABEL: Hermon Clotrimazole antifungal soap. bar
NDC: 85398-011 | Form: SOAP
Manufacturer: Beautivity LLC
Category: otc | Type: HUMAN OTC DRUG LABEL
Date: 20250821

ACTIVE INGREDIENTS: CLOTRIMAZOLE 1.16 g/116 g
INACTIVE INGREDIENTS: COCOS NUCIFERA (COCONUT) OIL; PROPYLENE GLYCOL; LAURIC ACID; MYRISTIC ACID; SODIUM MYRISTATE; SODIUM DODECYLBENZENESULFONATE; CERAMIDE 1; SORBITOL; OLEA EUROPAEA (OLIVE) FRUIT OIL; STEARIC ACID; MELALEUCA ALTERNIFOLIA (TEA TREE) LEAF OIL; GLYCERIN; AQUA; SODIUM GLUTAMATE; SODIUM HYDROXIDE; HAMAMELIS VIRGINIANA (WITCH HAZEL) LEAF WATER; ELAEIS GUINEENSIS (PALM) OIL

Initial Drug Listing - Hermon Clotrimazole antifungal soap bar

ACTIVE INGREDIENT

Clotrimazole 1%

PURPOSE

Antifungal

DOSAGE AND ADMINISTRATION

Proven clinically effective in the treatment of athlete's foot (tinea pedis), jock itch (tinea cruris), ringworm (tineacorporis). For effective relief of itching, irritation, redness, scaling, cracking, burning, soreness, and discomfort which can accompany these conditions.

WARNINGS

For external use only

DO NOT USE

children under 2 years of age unless directed by a doctor.

WHEN USING

avoide contact with eyes, lf contact occurs, rinse thoroughly with water.

STOP USE

irritation occurs or if there is no improvement within 2 weeks.

KEEP OUT OF REACH OF CHILDREN

If swallowed, get medical help or contact a Poison Control Center right away.

INDICATIONS AND USAGE

- Wet skin with warm water and lather soap.
- Gently massage onto affected areas.
- Rinse thoroughly and dry.
- Use twice daily or as directed by a doctor.

INACTIVE INGREDIENT

Melaleuca Alternifolia (Tea Tree) Leaf Oil, Aqua (Water), Sorbitol, Elaeis Guineensis (Palm) Oil, Cocos Nucifera (Coconut) Oil.Olea Europaea (0live) Fruit Oil, Propylene Glycol, Glycerin, Stearic Acid, Lauric Acid, Myristic Acid, Sodium Myristate, Sodium Glutamate, Sodium Hvdroxide, Sodium Dodecylbenzene Sulfonate, Sulfur Thermal Water, Hamamelis Virginiana (WitchHazel) Extract, Ceramide

STORAGE AND HANDLING

Store at room temperature. Protect from excessive heat (above 104°F/40°C)

QUESTIONS

visit us at www.hermonhealth.com